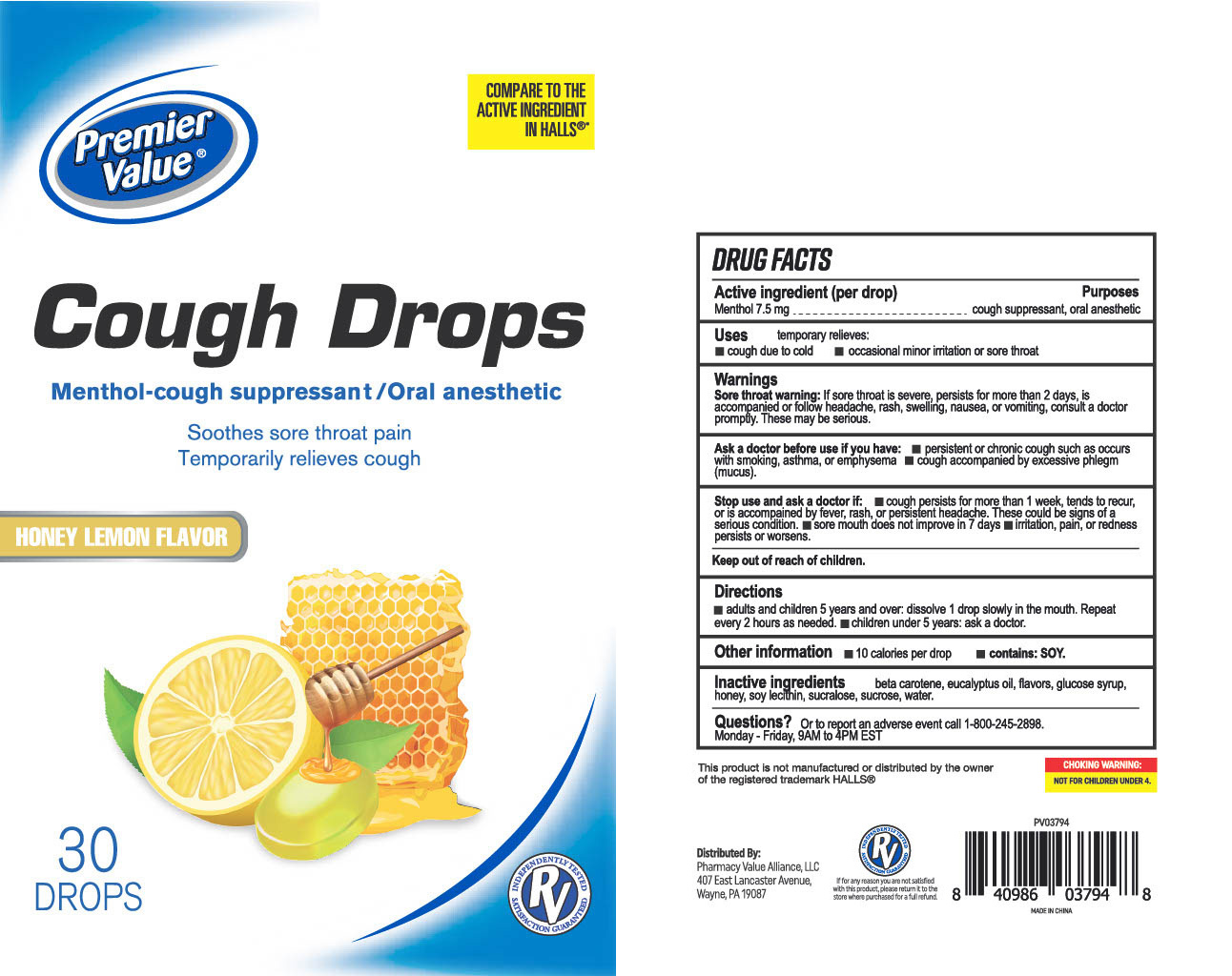 DRUG LABEL: Premier Value
NDC: 83698-884 | Form: LOZENGE
Manufacturer: Xiamen Kang Zhongyuan Biotechnology Co., Ltd.
Category: otc | Type: HUMAN OTC DRUG LABEL
Date: 20251229

ACTIVE INGREDIENTS: MENTHOL 7.5 mg/1 1
INACTIVE INGREDIENTS: SUCROSE; HONEY; BETA CAROTENE; EUCALYPTUS OIL; SUCRALOSE; CORN SYRUP; LECITHIN, SOYBEAN; WATER

PV-MGC-YNBY Honey Lemon Drops 30

Active Ingredient(s)

Menthol 7.5 mg

Purpose

Purposes cough suppressant, oral anesthetic

Use

temporary relieves: ■ cough due to cold ■ occasional minor irritation or sore throat

Warnings

Sore throat warning: If sore throat is severe, persists for more than 2 days, is accompanied or follow headache, rash, swelling, nausea, or vomiting, consult a doctor promptly. These may be serious.

Ask a doctor before use if you have: ■ persistent or chronic cough such as occurs with smoking, asthma, or emphysema ■ cough accompanied by excessive phlegm (mucus).

Stop use and ask a doctor if ■ cough persists for more than 1 week, tends to recur, or is accompained by fever, rash, or persistent headache. These could be signs of a serius condition. ■ sore mouth does not improve in 7 days ■ irritation, pain, or redness persists or worsens.

Keep out of reach of children.

Directions

■ adults and children 5 years and over: dissolve 1 drop slowly in the mouth. Repeat every 2 hours as needed.

■ children under 5 years: ask a doctor.

Other information

■ 10 calories per drop ■ contains: SOY.

Inactive ingredients

beta carotene, glucose syrup, sucrose, honey, eucalyptus oil, flavors, soy lecithin, sucralose, water.

QUESTIONS

Or, to report an adverse event, call 800-245-2898. Monday - Friday, 9 AM to APM EST

Package Label - Principal Display Panel

30 Drops NDC:61658-884-30